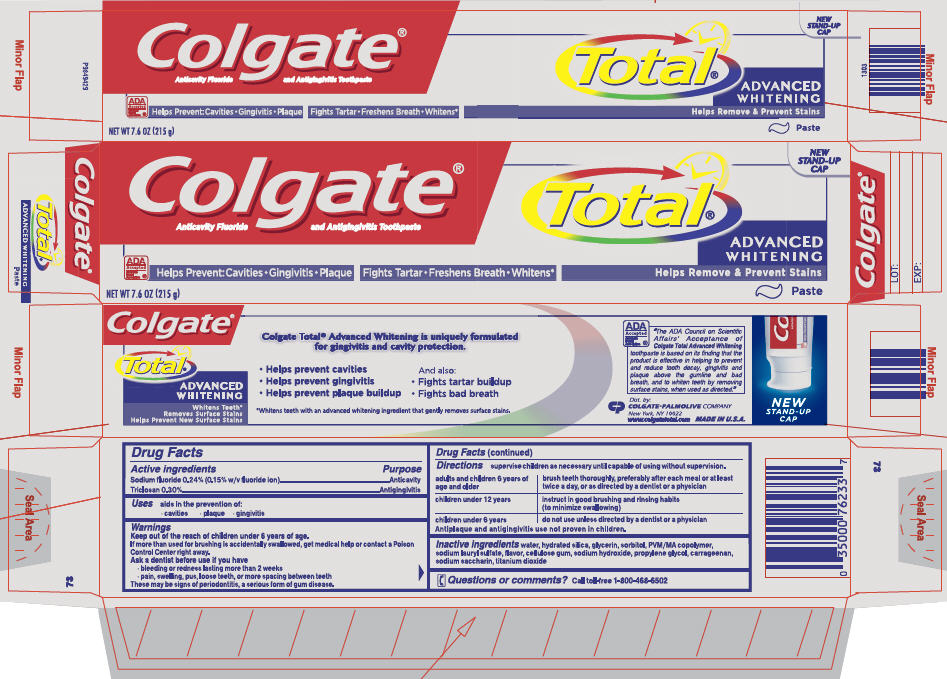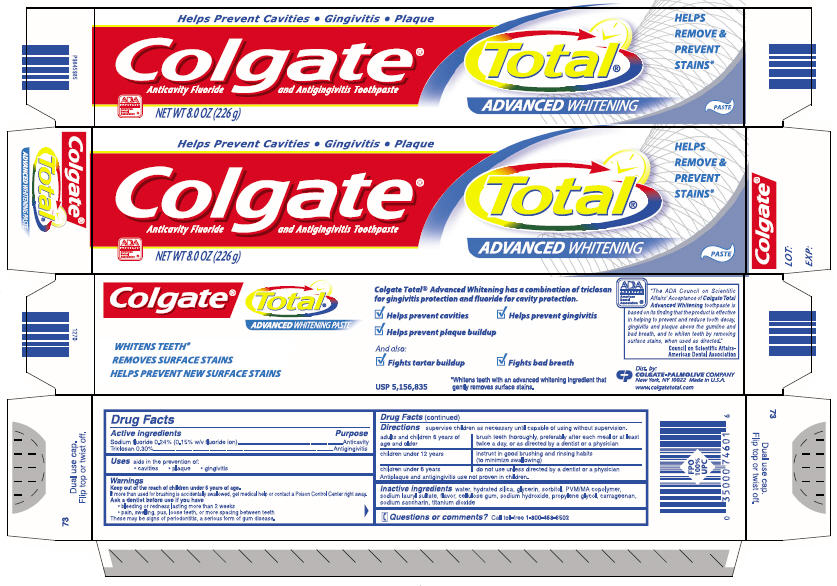 DRUG LABEL: Colgate
NDC: 67659-350 | Form: PASTE, DENTIFRICE
Manufacturer: Team Technologies, Inc
Category: otc | Type: HUMAN OTC DRUG LABEL
Date: 20180724

ACTIVE INGREDIENTS: SODIUM FLUORIDE 1.5 mg/1 g; TRICLOSAN 3 mg/1 g
INACTIVE INGREDIENTS: WATER; HYDRATED SILICA; GLYCERIN; SORBITOL; BUTYL ESTER OF METHYL VINYL ETHER/MALEIC ANHYDRIDE COPOLYMER (125000 MW); SODIUM LAURYL SULFATE; SODIUM HYDROXIDE; PROPYLENE GLYCOL; SACCHARIN SODIUM; CARBOXYMETHYLCELLULOSE SODIUM, UNSPECIFIED FORM; TITANIUM DIOXIDE; CARRAGEENAN

Colgate®
Anticavity Fluoride
and Antigingivitis Toothpaste

Active ingredients

Sodium fluoride 0.24% (0.15% w/v fluoride ion)

Triclosan 0.30%

Purpose

Anticavity

Antigingivitis

Uses

aids in the prevention of:

- cavities
- plaque
- gingivitis

Warnings

KEEP OUT OF REACH OF CHILDREN

Keep out of the reach of children under 6 years of age.

If more than used for brushing is accidentally swallowed, get medical help or contact a Poison Control Center right away.

Ask a dentist before use if you have

- bleeding or redness lasting more than 2 weeks
- pain, swelling, pus, loose teeth, or more spacing between teeth

These may be signs of periodontitis, a serious form of gum disease.

Directions

supervise children as necessary until capable of using without supervision.

adults and children 6 years of age and older | brush teeth thoroughly, preferably after each meal or at least twice a day, or as directed by a dentist or a physician
children under 12 years | instruct in good brushing and rinsing habits (to minimize swallowing)
children under 6 years | do not use unless directed by a dentist or a physician

Antiplaque and antigingivitis use not proven in children.

Inactive ingredients

water, hydrated silica, glycerin, sorbitol, PVM/MA copolymer, sodium lauryl sulfate, flavor, cellulose gum, sodium hydroxide, propylene glycol, carrageenan, sodium saccharin, titanium dioxide

Questions or comments?

Call toll-free 1-800-468-6502

Dist. by:
COLGATE-PALMOLIVE COMPANY
New York, NY 10022 Made in U.S.A.
www.colgatetotal.com

PRINCIPAL DISPLAY PANEL - 226 g Tube

Helps Prevent Cavities • Gingivitis • Plaque

Colgate®
Total®
Anticavity Fluoride and Antigingivitis Toothpaste

ADVANCED WHITENING
PASTE

HELPS
REMOVE &
PREVENT
STAINS*

ADA
ACCEPTED
American
Dental
Association ®

NET WT 8.0 OZ (226 g)

PRINCIPAL DISPLAY PANEL - 226 g carton

Helps Prevent Cavities • Gingivitis • Plaque

Colgate®
Total®
Anticavity Fluoride and Antigingivitis Toothpaste

ADVANCED WHITENING
PASTE

HELPS
REMOVE &
PREVENT
STAINS*

ADA
ACCEPTED
American
Dental
Association ®

NET WT 8.0 OZ (226 g)